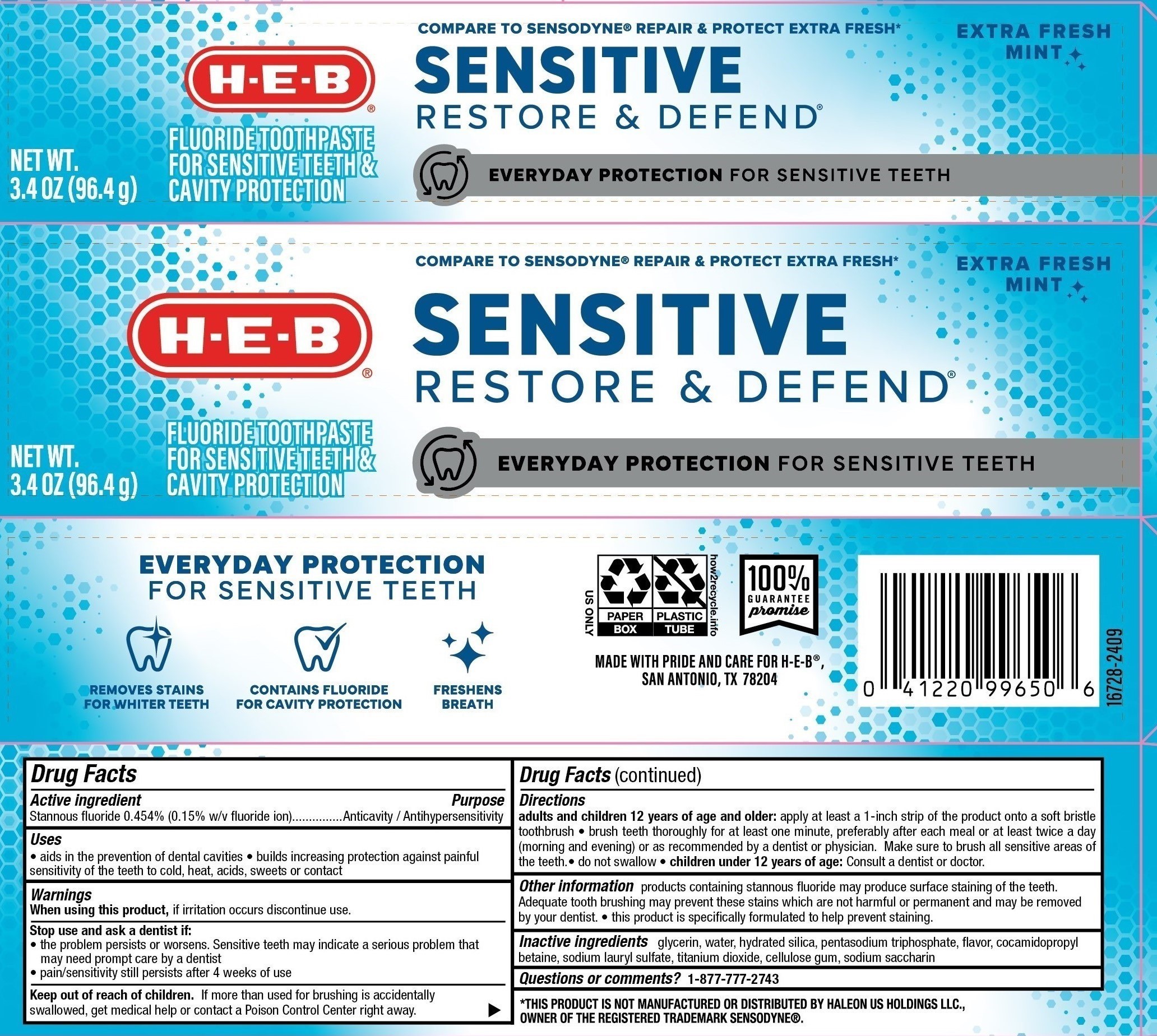 DRUG LABEL: H E B
NDC: 37808-230 | Form: PASTE, DENTIFRICE
Manufacturer: HEB
Category: otc | Type: HUMAN OTC DRUG LABEL
Date: 20250808

ACTIVE INGREDIENTS: STANNOUS FLUORIDE 0.15 g/100 g
INACTIVE INGREDIENTS: SORBITOL; GLYCERIN; SACCHARIN SODIUM; WATER; TITANIUM DIOXIDE; SODIUM TRIPOLYPHOSPHATE ANHYDROUS; CARBOXYMETHYLCELLULOSE SODIUM; COCAMIDOPROPYL BETAINE; SODIUM LAURYL SULFATE; HYDRATED SILICA

5820230, 5820273 HEB Sensitive Restore and Defend

Drug Facts

Active ingredients

Stannous Fluoride 0.454% (0.15% w/v fluoride ion)

Purpose

Anticavity/Antihypersensitivity

Uses

- aids in the prevention of dental cavities
- builds increasing protection against painful sensitivity of the teeth to cold, heat, acids sweets or contact

Warnings

When using this product, if irritation occurs discontinue use.

Stop use and ask a dentist if:

- the problem persists or worsens. Sensitive teeth may indicate a serious problem that may need prompt care by a dentist.
- pain/sensitivity still persists after 4 weeks of use

Keep out of reach of children. If more than used for brushing is accidentally swallowed, get medical help or contact a Poison Control Center right away.

Directions

Adults and children 12 years of age and older: Apply at least a 1-inch strip of the product onto a soft bristle toothbrush.

- Brush teeth thoroughly for at least one minute, preferably after each meal or at least twice a day (morning and evening) or as directed by a dentist or physician. Make sure to brush all sensitive areas of the teeth.
- Do not swallow.
- Children under 12 years of age: consult a dentist or doctor.

INACTIVE INGREDIENT

Inactive ingredients glycerin, water, hydrated silica, pentasodium triphosphate, flavor, cocamidopropyl betaine, sodium lauryl sulfate, titanium dioxide, cellulose gum, sodium saccharin

Questions or Comments? CALL 1-877-777-2743

MADE WITH PRIDE AND CARE FOR H-E-B®

SAN ANTONIO, TX 78204

Other information products containng stannous fluoride may produce surface staining of the teeth. Adequate tooth brushing may prevent these stains which are not harmful or permanent and may be removed by your dentist.

- this product is specifically formulated to help prevent staining.